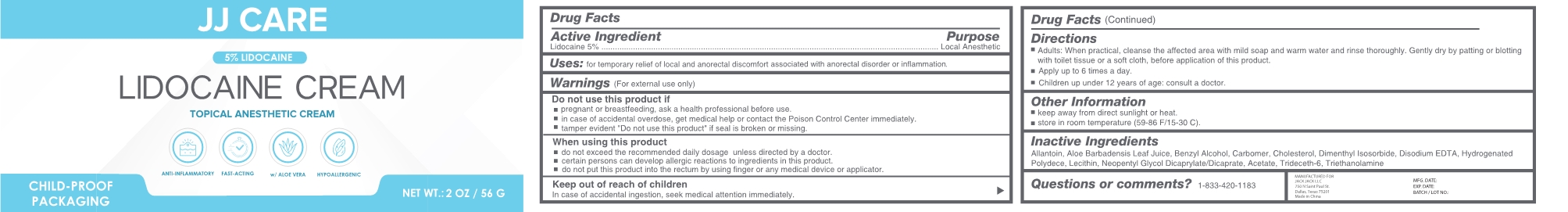 DRUG LABEL: LIDOCAINE
NDC: 83365-003 | Form: CREAM
Manufacturer: Sichuan Gumo Brand Management Co.,Ltd
Category: otc | Type: HUMAN OTC DRUG LABEL
Date: 20230421

ACTIVE INGREDIENTS: LIDOCAINE 5 g/100 g
INACTIVE INGREDIENTS: PROPYLENE GLYCOL; WATER; SODIUM POLYACRYLATE (2500000 MW); ALLANTOIN; EDETATE DISODIUM ANHYDROUS; HYDROGENATED POLYDECENE TYPE I; LECITHIN, SOYBEAN; NEOPENTYL GLYCOL DICAPRYLATE/DICAPRATE; TROLAMINE; ALPHA-TOCOPHEROL; TRIDECETH-6; ALOE VERA LEAF; CARBOMER HOMOPOLYMER, UNSPECIFIED TYPE; DIMETHYL ISOSORBIDE; BENZYL ALCOHOL; CHOLESTEROL

83365-003

Active Ingredient

Lidocaine 5%

Purpose

Local Anesthetic

Uses

for temporary relief of local and anorectal discomfort associated with anorectal disorder or inflammation

Warnings

Warnings (For extemal use only)

When using this product

do not exceed the recommended daily dosage unless directed by a doctor.

certain persons can develop allergic reactions to ingredients in this product.

do not put this product into the rectum by using finger or any medical device or applicator.

Stop use

n/a

Keep out of reach of children

Incase of accidental ingestion , seek medical attention immediately

Directions

Adults : When practical , cleanse the affected area with mild soap and warm water and rinse thoroughly. Gently dry by patting or blottingwith toilet tissue or a soft cloth , before application of this product.

Apply up to 6 times a day,

Children up under 12 years of age: consult a doctor.

Other Information

keep away from direct sunlight or heata.

store in room temperature (59-86 F/15-30 C)

Inactive Ingredients

Allantoin, Aloe Barbadensis Leaf Juice, Benzyl Alcohol, Carbomer, Cholesterol, Dimenthyl Isosorbide, Disodium EDTA , Hydrogenated Polydece, Lecithin, Neopentyl Glycol Dicaprylate/Dicaprate, Acetate, Trideceth-6, Triethanolamine